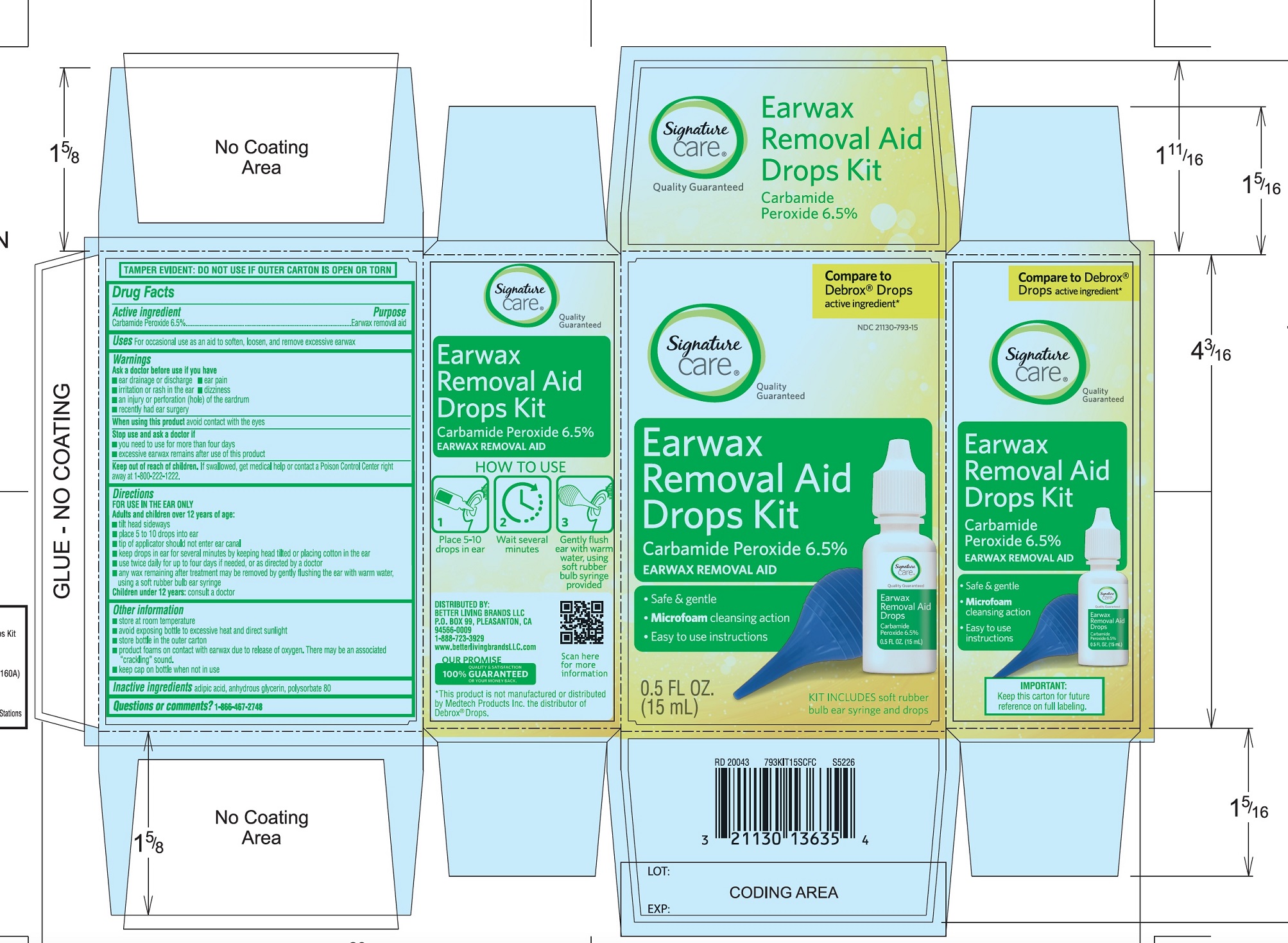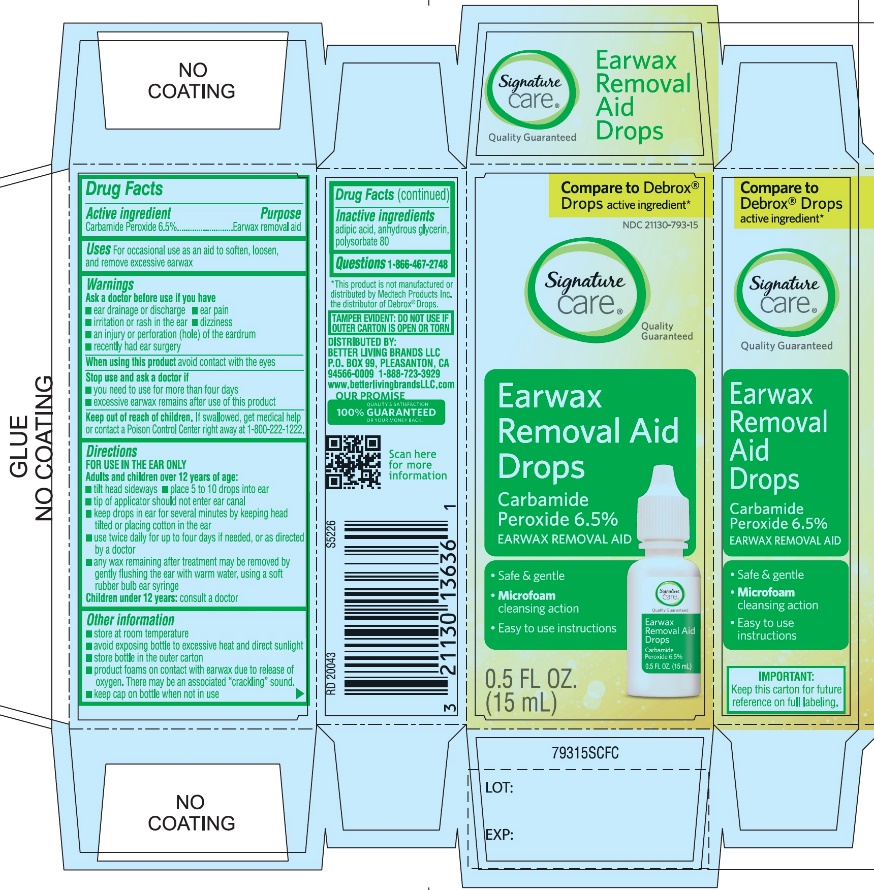 DRUG LABEL: Ear Wax Removal Aid Drops
NDC: 21130-793 | Form: LIQUID
Manufacturer: BETTER LIVING BRANDS, LLC
Category: otc | Type: HUMAN OTC DRUG LABEL
Date: 20251029

ACTIVE INGREDIENTS: CARBAMIDE PEROXIDE 65 mg/1 mL
INACTIVE INGREDIENTS: ADIPIC ACID; GLYCERIN; POLYSORBATE 80

Ear Wax Removal Aid Drops

Drug Facts

Active ingredient

Carbamide peroxide 6.5%

Purpose

Earwax removal aid

Uses

For occasional use as an aid to soften, loosen and remove excessive ear wax

Warnings

Ask a doctor before use

- if you have ear drainage or discharge
- ear pain
- irritation or rash in the ear
- dizziness
- an injury or perforation (hole) of the eardrum
- recently had ear surgery

When using this product

avoid contact with the eyes

Stop use and ask a doctor if

- you need to use for more than four days
- excessive ear wax remains after use this product

Keep out of reach of children.

If swallowed, get medical help or contact a Poison Control Center (1-800-222-1222) right away.

Directions

FOR USE IN THE EAR ONLY.

- Adults and children over 12 years of age:
- tilt head sideways
- place 5 to 10 drops into ear canal.
- tip of applicator should not enter ear canal.
- keep drops in ear for several minutes by keeping head tilted or placing cotton in the ear.
- use twice daily for up to 4 days if needed, or as directed by a doctor.
- any wax remaining after treatment may be removed by gently flushing the ear with warm water, using a soft rubber bulb ear syringe.

Children under 12 years of age:consult a doctor.

Other information

- store at room temperature
- avoid exposing bottle to excessive heat and direct sunlight
- store bottle in the outer carton
- product foams on contact with earwax due to release of oxygen. There may be an associated “cracking” sound.
- keep cap on bottle when not in use

Inactive ingredients

adipic acid, anhydrous glycerin, polysorbate 80

PRINCIPAL DISPLAY PANEL

*Compare to the active ingredient in Debrox®Drops

NDC 21130-793-15

Ear Wax Removal Aid Drops
Carbamide Peroxide 6.5%

Ear Wax Removal Aid

- Safe & Gentle
- Microfoam Cleansing Action
- Easy to use Instructions

NET WT 0.5 FL OZ (15 mL)

TAMPER EVIDENT: DO NOT USE IF OUTER CARTON IS OPEN OR TORN

DISTRIBUTED BY BETTER LIVING BRANDS LLC

P.O. BOX 99, PLEASANTON, CA 94566-0009

1-888-723-3929

www.betterlivingbrandsLLC.com

IMPORTANT:Keep this carton for future labeling.

*This product is not manufactured or distributed by Medtech Products Inc. the distributor of Debrox®Drops.